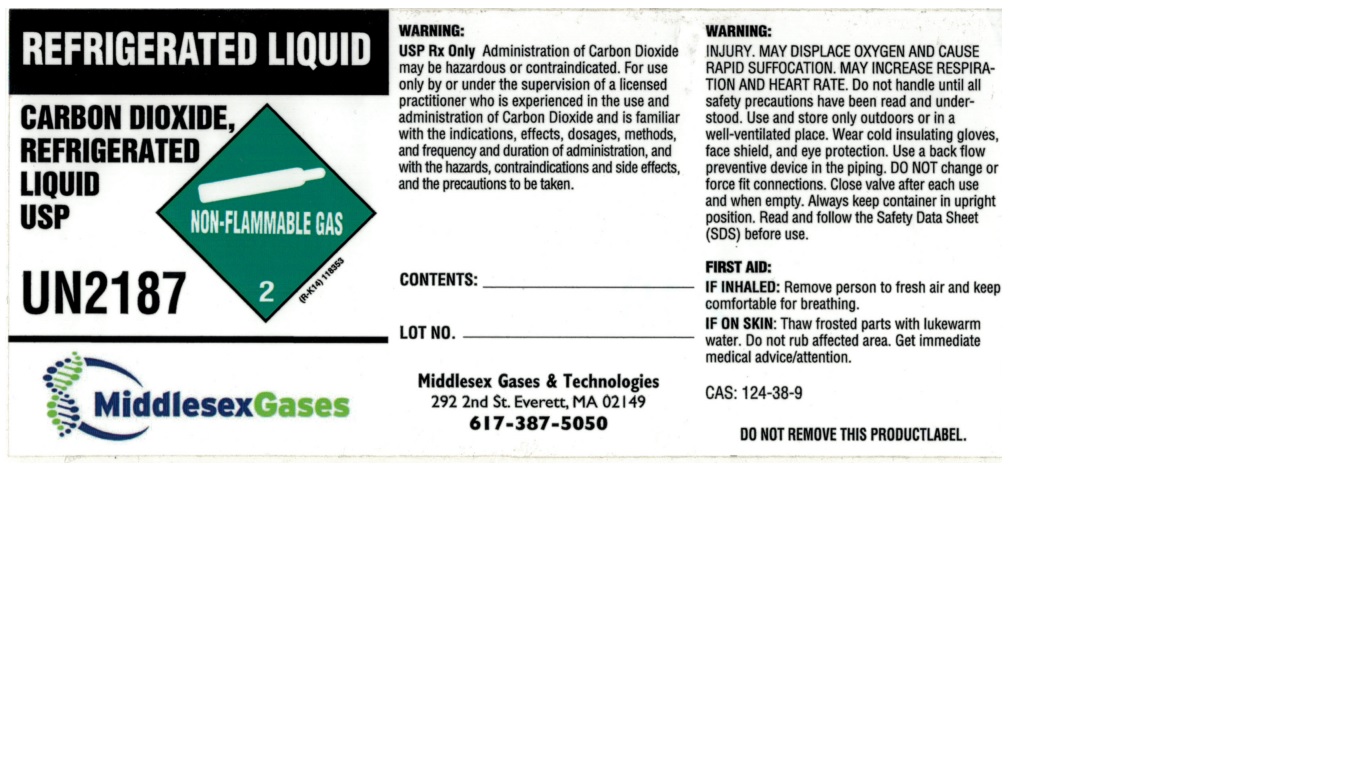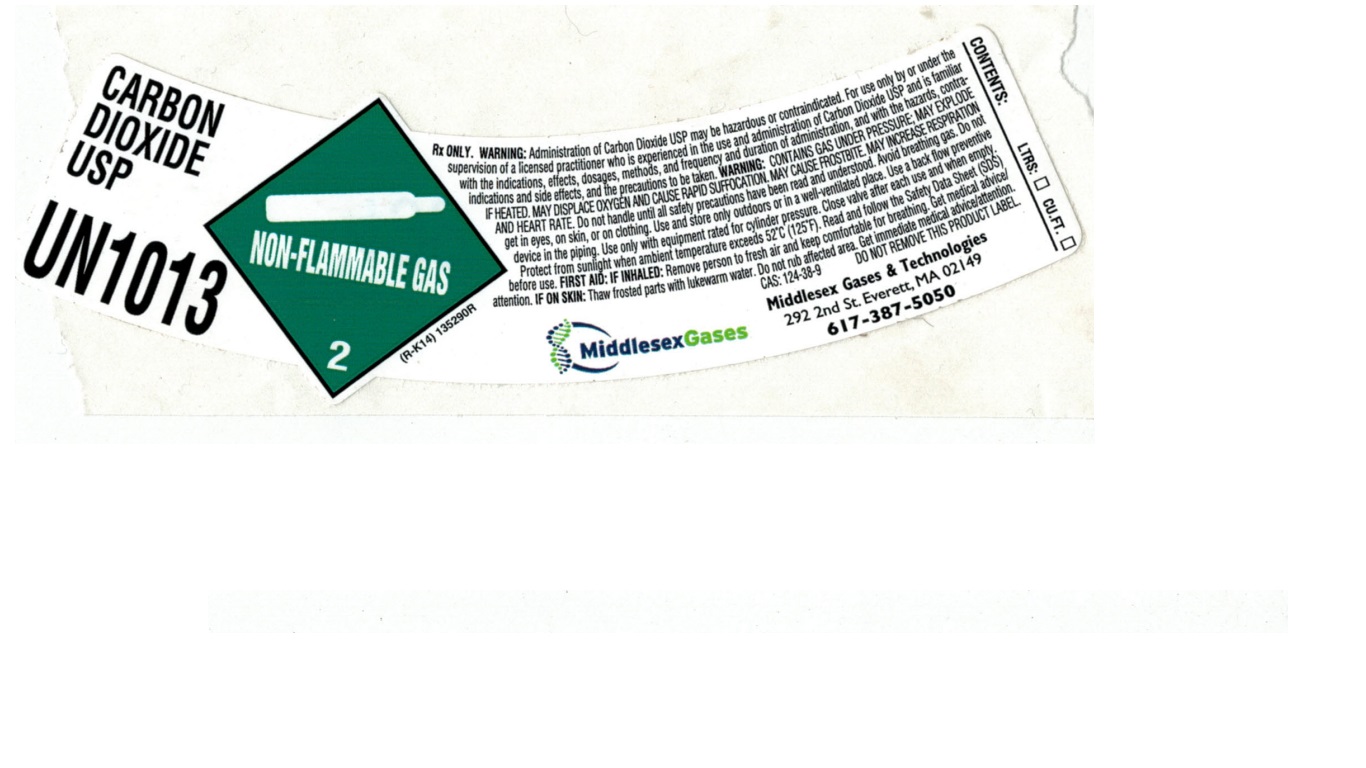 DRUG LABEL: Carbon Dioxide
NDC: 63961-010 | Form: GAS
Manufacturer: Middlesex Gases & Technologies, Inc.
Category: prescription | Type: HUMAN PRESCRIPTION DRUG LABEL
Date: 20241107

ACTIVE INGREDIENTS: CARBON DIOXIDE 998 mL/1 L

Carbon Dioxide

PACKAGE LABEL

REFRIGERATED LIQUID

CARBON DIOXIDE, REFRIGERATED LIQUID USP

UN2187

MiddlesexGases

WARNING:

USP Rx Only Administration of Carbon Dioxide may be hazardous or contraindicated. For use only by or under the supervision of a licensed practitioner who is experienced in the use and administration of Carbon Dioxide and is familiar with the indications, effects, dosages, methods, and frequency and duration of administration, and with the hazards, contraindications and side effects, and the precautions to be taken.

CONTENTS:

LOT NO.

Middlesex Gases & Technologies 292 2nd St. Everett, MA 02149

617-387-5050

WARNING:

INJURY. MAY DISPLACE OXYGEN AND CAUSE RAPID SUFFOCATION. MAY INCREASE RESPIRATION AND HEART RATE. Do not handle until all safety precautions have been read and understood. Use and store only outdoors or in a well-ventilated place. Wear cold insulating gloves, face shield, and eye protection. Use a back flow preventive device in the piping. DO NOT change or force fit connections. Close valve after each use and when empty. Always keep container in upright position. Read and follow the Safety Data Sheet (SDS) before use.

FIRST AID:

IF INHALED: Remove person to fresh air and keep comfortable for breathing.

IF ON SKIN: Thaw frosted parts with lukewarm water. Do not rub affected area. Get immediate medical advice/attention.

CAS: 124-38-9

DO NOT REMOVE THIS PRODUCT LABEL.

PACKAGE LABEL

CARBON DIOXIDE USP

UN1013

Rx ONLY. WARNING: Administration of Carbon Dioxide USP may be hazardous or contraindicated. For use only by or under the supervision of a licensed practitioner who is experienced in the use and administration of Carbon Dioxide USP and is familiar with the indications, effects, dosages, methods, and frequency and duration of administration, and with the hazards, contraindications and side effects, and the precautions to be taken. WARNING: CONTAINS GAS UNDER PRESSURE; MAY EXPLODE IF HEATED. MAY DISPLACE OXYGEN AND CAUSE RAPID SUFFOCATION. MAY CAUSE FROSTBITE. MAY INCREASE RESPIRATION AND HEART RATE. Do not handle until all safety precautions have been read and understood. Avoid breathing gas. Do not get in eyes, on skin, or on clothing. Use and store only outdoors or in a well-ventilated place. Use a back flow preventive device in the piping. Use only with equipment rated for cylinder pressure. Close valve after each use and when empty. Protect from sunlight when ambient temperature exceeds 52 C (125 F). Read and follow the Safety Data Sheet (SDS) before use. FIRST AID: IF INHALED: Remove person to fresh air and keep comfortable for breathing. Get medical advice/attention. IF ON SKIN: Thaw frosted parts with lukewarm water. Do not rub affected area. Get immediate medical advice/attention.

CAS: 124-38-9 DO NOT REMOVE THIS PRODUCT LABEL.

MiddlesexGases

Middlesex Gases & Technologies

292 2nd St. Everett, MA 02149

617-387-5050

CONTENTS: LTRS: CU.FT.